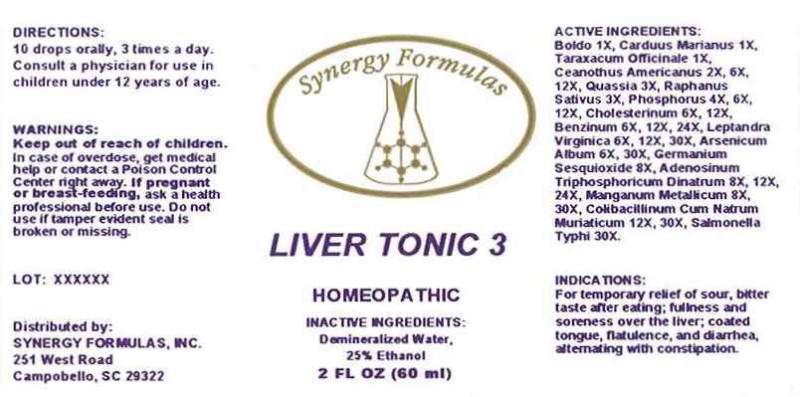 DRUG LABEL: Liver Tonic
NDC: 43772-0033 | Form: LIQUID
Manufacturer: Synergy Formulas, Inc.
Category: homeopathic | Type: HUMAN OTC DRUG LABEL
Date: 20150306

ACTIVE INGREDIENTS: PEUMUS BOLDUS LEAF 1 [hp_X]/1 mL; MILK THISTLE 1 [hp_X]/1 mL; TARAXACUM OFFICINALE 1 [hp_X]/1 mL; CEANOTHUS AMERICANUS LEAF 2 [hp_X]/1 mL; QUASSIA AMARA WOOD 3 [hp_X]/1 mL; RADISH 3 [hp_X]/1 mL; PHOSPHORUS 4 [hp_X]/1 mL; CHOLESTEROL 6 [hp_X]/1 mL; BENZENE 6 [hp_X]/1 mL; VERONICASTRUM VIRGINICUM ROOT 6 [hp_X]/1 mL; ARSENIC TRIOXIDE 6 [hp_X]/1 mL; GERMANIUM SESQUIOXIDE 8 [hp_X]/1 mL; ADENOSINE TRIPHOSPHATE DISODIUM 8 [hp_X]/1 mL; MANGANESE 8 [hp_X]/1 mL; ESCHERICHIA COLI 12 [hp_X]/1 mL; SALMONELLA ENTERICA SUBSP. ENTERICA SEROVAR TYPHI 30 [hp_X]/1 mL
INACTIVE INGREDIENTS: WATER; ALCOHOL

Drug Facts:

ACTIVE INGREDIENTS:

Boldo 1X, Carduus Marianus 1X, Taraxacum Officinale 1X, Ceanothus Americanus 2X, 6X, 12X, Quassia (Amara) 3X, Raphanus Sativus 3X, Phosphorus 4X, 6X, 12X, Cholesterinum 6X, Benzinum 6X, 12X, 24X, Leptandra Virginica 6X, 12X, 30X, Arsenicum Album 6X, 30X, Germanium Sesquioxide 8X, Adenosinum Triphosphoricum Dinatrum 8X, 12X, 24X, Manganum Metallicum 8X, 30X, Colibacillinum Cum Natrum Muriaticum 12X, 30X, Salmonella Typhi 30X

INDICATIONS:

For temporary relief of sour, bitter taste after eating; fullness and soreness over the liver; coated tongue, flatulence and diarrhea, alternating with constipation.

WARNINGS:

Keep out of reach of children. In case of overdose, get medidcal help or contact a Poison Control Center right away.

If pregnant or breast-feeding, ask a health professional before use.

Do not use if tamper evident seal is broken or missing.

Keep out of reach of children. In case of overdose, get medical help or contact a Poison Control Center right away.

DIRECTIONS:

10 drops orally, 3 times a day. Consult a physician for use in children under 12 years of age.

INDICATIONS:

For temporary relief of sour, bitter taste after eating; fullness and soreness over the liver; coated tongue, flatulence and diarrhea, alternating with constipation.

INACTIVE INGREDIENTS:

Demineralized Water, 25% Ethanol

QUESTIONS:

Distributed by:

SYNERGY FORMULAS, INC.

251 West Road

Campobello, SC 29322

PACKAGE LABEL DISPLAY:

Synergy Formulas

LIVER TONIC 3

HOMEOPATHIC

2 FL OZ (60 ml)